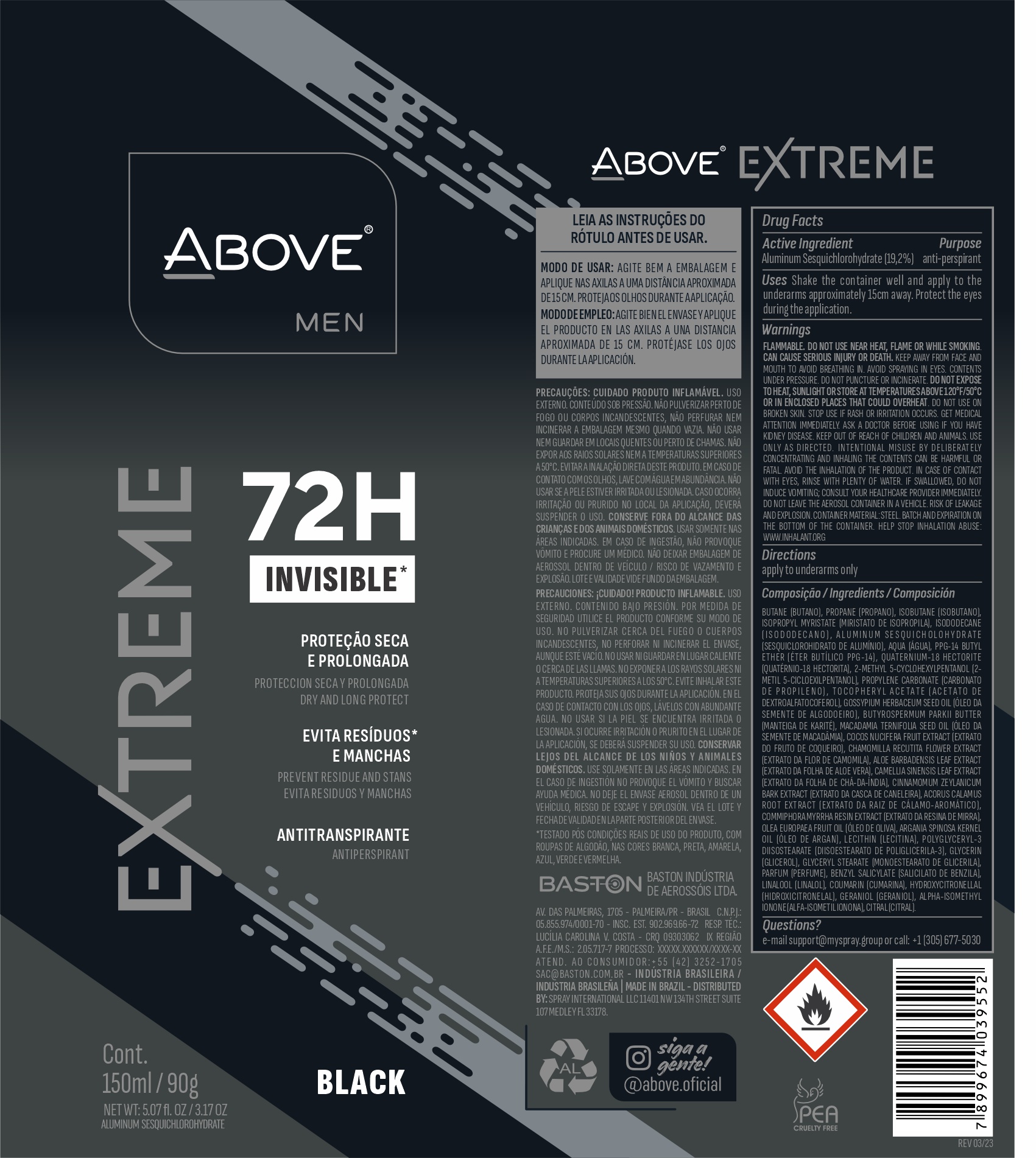 DRUG LABEL: ABOVE EXTREME MEN BLACK 72 HOURS
NDC: 73306-1159 | Form: AEROSOL, SPRAY
Manufacturer: BASTON INDUSTRIA DE AEROSSOIS LTDA
Category: otc | Type: HUMAN OTC DRUG LABEL
Date: 20241009

ACTIVE INGREDIENTS: ALUMINUM SESQUICHLOROHYDRATE 19 mg/90 g
INACTIVE INGREDIENTS: ISOBUTANE

ABOVE EXTREME MEN BLACK 72 HOURS SPRAY

BUTANE (BUTANO) PROPANE (PROPANO) ISOBUTANE (ISOBUTANO) ISOPROPYL MYRISTATE (MIRISTATO DE ISOPROPILA) ISODODECANE (ISODODECANO) AQUA (ÁGUA) PPG-14 BUTYL ETHER (ÉTER BUTÍLICO PPG-14) PARFUM (PERFUME) QUATERNIUM-18 HECTORITE (QUATÉRNIO-18 HECTORITA) 2-METHYL 5-CYCLOHEXYLPENTANOL (2-METIL 5-CICLOEXILPENTANOL) PROPYLENE CARBONATE (CARBONATO DE PROPILENO) TOCOPHERYL ACETATE (ACETATO DE DEXTROALFATOCOFEROL) GOSSYPIUM HERBACEUM SEED OIL (ÓLEO DA SEMENTE DE ALGODOEIRO) BUTYROSPERMUM PARKII BUTTER (MANTEIGA DE KARITÉ) MACADAMIA TERNIFOLIA SEED OIL (ÓLEO DA SEMENTE DE MACADÂMIA) COCOS NUCIFERA FRUIT EXTRACT (EXTRATO DO FRUTO DE COQUEIRO) CHAMOMILLA RECUTITA FLOWER EXTRACT (EXTRATO DA FLOR DE CAMOMILA) ALOE BARBADENSIS LEAF EXTRACT (EXTRATO DA FOLHA DE ALOE VERA) CAMELLIA SINENSIS LEAF EXTRACT (EXTRATO DA FOLHA DE CHÁ-DA-ÍNDIA) CINNAMOMUM ZEYLANICUM BARK EXTRACT (EXTRATO DA CASCA DE CANELEIRA) ACORUS CALAMUS ROOT EXTRACT (EXTRATO DA RAIZ DE CÁLAMO-AROMÁTICO) COMMIPHORA MYRRHA RESIN EXTRACT (EXTRATO DA RESINA DE MIRRA) OLEA EUROPAEA FRUIT OIL (ÓLEO DE OLIVA) ARGANIA SPINOSA KERNEL OIL (ÓLEO DE ARGAN) LECITHIN (LECITINA) POLYGLYCERYL-3 DIISOSTEARATE (DIISOESTEARATO DE POLIGLICERILA-3) GLYCERIN (GLICEROL) GLYCERYL STEA

BUTANE (BUTANO)
PROPANE (PROPANO)
ISOBUTANE (ISOBUTANO)
ISOPROPYL MYRISTATE (MIRISTATO DE ISOPROPILA)
ISODODECANE (ISODODECANO)
AQUA (ÁGUA)
PPG-14 BUTYL ETHER (ÉTER BUTÍLICO PPG-14)
PARFUM (PERFUME)
QUATERNIUM-18 HECTORITE (QUATÉRNIO-18 HECTORITA)
2-METHYL 5-CYCLOHEXYLPENTANOL (2-METIL 5-CICLOEXILPENTANOL)
PROPYLENE CARBONATE (CARBONATO DE PROPILENO)
TOCOPHERYL ACETATE (ACETATO DE DEXTROALFATOCOFEROL)
GOSSYPIUM HERBACEUM SEED OIL (ÓLEO DA SEMENTE DE ALGODOEIRO)
BUTYROSPERMUM PARKII BUTTER (MANTEIGA DE KARITÉ)
MACADAMIA TERNIFOLIA SEED OIL (ÓLEO DA SEMENTE DE MACADÂMIA)
COCOS NUCIFERA FRUIT EXTRACT (EXTRATO DO FRUTO DE COQUEIRO)
CHAMOMILLA RECUTITA FLOWER EXTRACT (EXTRATO DA FLOR DE CAMOMILA)
ALOE BARBADENSIS LEAF EXTRACT (EXTRATO DA FOLHA DE ALOE VERA)
CAMELLIA SINENSIS LEAF EXTRACT (EXTRATO DA FOLHA DE CHÁ-DA-ÍNDIA)
CINNAMOMUM ZEYLANICUM BARK EXTRACT (EXTRATO DA CASCA DE CANELEIRA)
ACORUS CALAMUS ROOT EXTRACT (EXTRATO DA RAIZ DE CÁLAMO-AROMÁTICO)
COMMIPHORA MYRRHA RESIN EXTRACT (EXTRATO DA RESINA DE MIRRA)
OLEA EUROPAEA FRUIT OIL (ÓLEO DE OLIVA)
ARGANIA SPINOSA KERNEL OIL (ÓLEO DE ARGAN)
LECITHIN (LECITINA)
POLYGLYCERYL-3 DIISOSTEARATE (DIISOESTEARATO DE POLIGLICERILA-3)
GLYCERIN (GLICEROL)
GLYCERYL STEARATE (MONOESTEARATO DE GLICERILA)